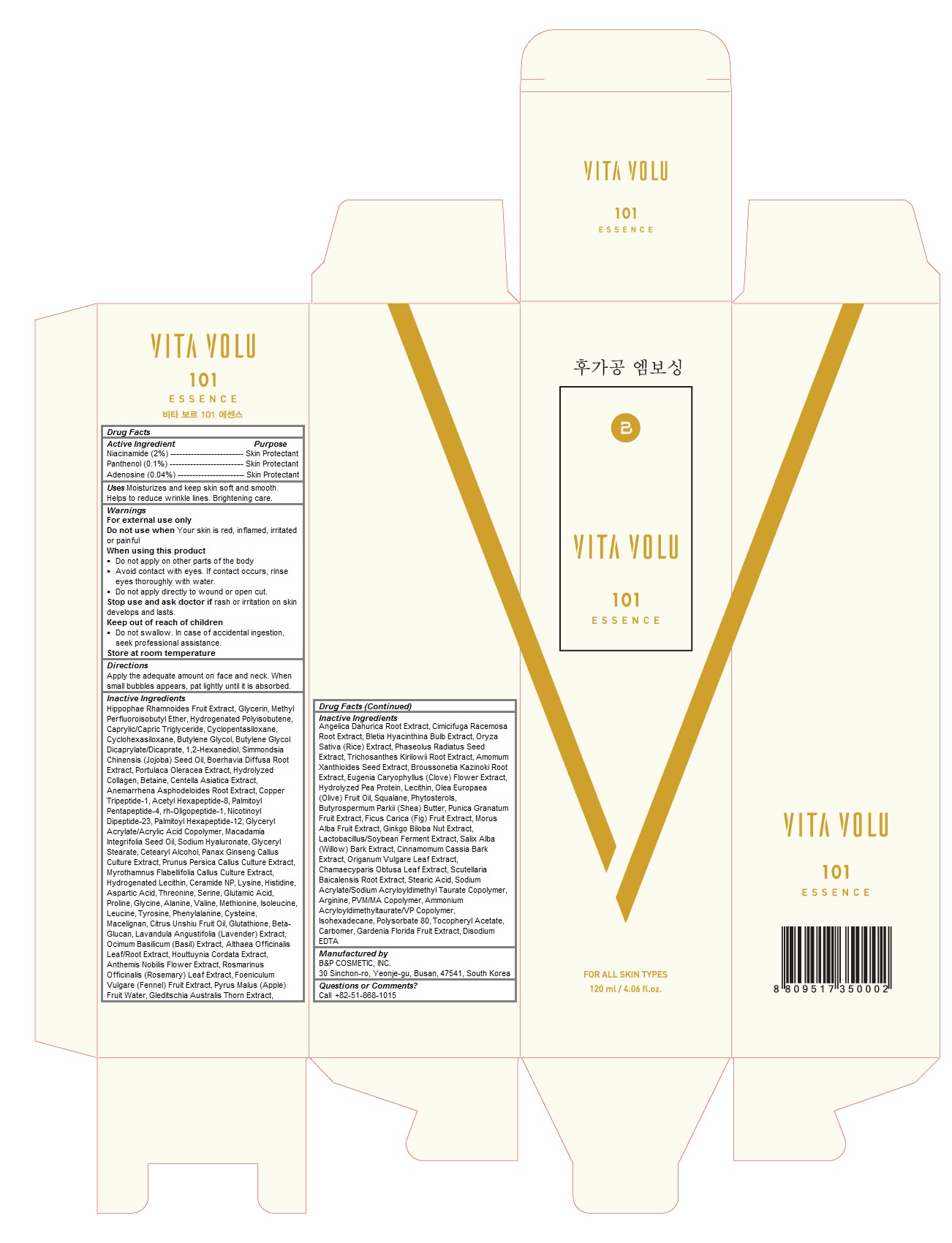 DRUG LABEL: VITA VOLU 101 ESSENCE
NDC: 71294-101 | Form: LIQUID
Manufacturer: B&P COSMETIC, INC.
Category: otc | Type: HUMAN OTC DRUG LABEL
Date: 20170303

ACTIVE INGREDIENTS: Niacinamide 2.4 g/120 mL; PANTHENOL 0.12 g/120 mL; ADENOSINE 0.04 g/120 mL
INACTIVE INGREDIENTS: HIPPOPHAE RHAMNOIDES FRUIT; Glycerin; METHYL PERFLUOROISOBUTYL ETHER; HYDROGENATED POLYBUTENE (1300 MW); MEDIUM-CHAIN TRIGLYCERIDES; CYCLOMETHICONE 5; CYCLOMETHICONE 6; Butylene Glycol; BUTYLENE GLYCOL DICAPRYLATE/DICAPRATE; 1,2-Hexanediol; JOJOBA OIL; BOERHAVIA DIFFUSA ROOT; PURSLANE; Betaine; CENTELLA ASIATICA; ANEMARRHENA ASPHODELOIDES ROOT; PREZATIDE COPPER; ACETYL HEXAPEPTIDE-8; PALMITOYL PENTAPEPTIDE-4; NEPIDERMIN; PALMITOYL HEXAPEPTIDE-12; MACADAMIA OIL; HYALURONATE SODIUM; GLYCERYL MONOSTEARATE; CETOSTEARYL ALCOHOL; ASIAN GINSENG; PEACH; MYROTHAMNUS FLABELLIFOLIA WHOLE; HYDROGENATED SOYBEAN LECITHIN; Ceramide NP; Lysine; Histidine; ACETYL ASPARTIC ACID; Threonine; Serine; Glutamic Acid; Proline; Glycine; Alanine; Valine; Methionine; Isoleucine; Leucine; Tyrosine; Phenylalanine; Cysteine; Macelignan; CITRUS RETICULATA FRUIT OIL; Glutathione; LAVANDULA ANGUSTIFOLIA SUBSP. ANGUSTIFOLIA FLOWERING TOP; OCIMUM BASILICUM FLOWERING TOP; ALTHAEA OFFICINALIS LEAF; HOUTTUYNIA CORDATA FLOWERING TOP; CHAMAEMELUM NOBILE FLOWER; ROSEMARY; FENNEL SEED; APPLE FRUIT OIL; ANGELICA DAHURICA ROOT; BLACK COHOSH; BLETILLA STRIATA TUBER; RICE GERM; MUNG BEAN; TRICHOSANTHES KIRILOWII ROOT; AMOMUM VILLOSUM SEED; BROUSSONETIA KAZINOKI ROOT; CLOVE; EGG PHOSPHOLIPIDS; OLIVE OIL; Squalane; .BETA.-SITOSTEROL; SHEA BUTTER; POMEGRANATE; FIG; WHITE MULBERRY; GINKGO BILOBA SEED; SALIX ALBA BARK; CHINESE CINNAMON; OREGANO; CHAMAECYPARIS OBTUSA LEAF; SCUTELLARIA BAICALENSIS ROOT; Stearic Acid; SODIUM ACRYLATE/SODIUM ACRYLOYLDIMETHYLTAURATE COPOLYMER (4000000 MW); Arginine; AMMONIUM ACRYLOYLDIMETHYLTAURATE/VP COPOLYMER; ISOHEXADECANE; POLYSORBATE 80; .ALPHA.-TOCOPHEROL ACETATE; CARBOXYPOLYMETHYLENE; GARDENIA JASMINOIDES FRUIT; EDETATE DISODIUM

VITA VOLU 101 ESSENCE

Acitive Ingredients

Niacinamide (2%)

Panthenol (0.1%)

Adenosine (0.04%)

Purpose

Skin protectant

Keep out of reach of children

 Do not swallow. In case of accidental ingestion, seek professional assistance

Uses

Moisturizes and keep skin soft and smooth. Helps to reduce wrinkle lines. Brightening care.

Warnings

For external use only
Do not use when Your skin is red, inflamed, irritated or painful
When using this product
 Do not apply on other parts of the body
 Avoid contact with eyes. If contact occurs, rinse eyes thoroughly with water.
 Do not apply directly to wound or open cut.
Stop use and ask doctor if rash or irritation on skin develops and lasts.

Store at room temperature

Directions

Apply the adequate amount on face and neck. When small bubbles appears, pat lightly until it is absorbed.

Inactive Ingredients

Hippophae Rhamnoides Fruit Extract, Glycerin, Methyl Perfluoroisobutyl Ether, Hydrogenated Polyisobutene, Caprylic/Capric Triglyceride, Cyclopentasiloxane, Cyclohexasiloxane, Butylene Glycol, Butylene Glycol Dicaprylate/Dicaprate, 1,2-Hexanediol, Simmondsia Chinensis (Jojoba) Seed Oil, Boerhavia Diffusa Root Extract, Portulaca Oleracea Extract, Hydrolyzed Collagen, Betaine, Centella Asiatica Extract, Anemarrhena Asphodeloides Root Extract, Copper Tripeptide-1, Acetyl Hexapeptide-8, Palmitoyl Pentapeptide-4, rh-Oligopeptide-1, Nicotinoyl Dipeptide-23, Palmitoyl Hexapeptide-12, Glyceryl Acrylate/Acrylic Acid Copolymer, Macadamia Integrifolia Seed Oil, Sodium Hyaluronate, Glyceryl Stearate, Cetearyl Alcohol, Panax Ginseng Callus Culture Extract, Prunus Persica Callus Culture Extract, Myrothamnus Flabellifolia Callus Culture Extract, Hydrogenated Lecithin, Ceramide NP, Lysine, Histidine, Aspartic Acid, Threonine, Serine, Glutamic Acid, Proline, Glycine, Alanine, Valine, Methionine, Isoleucine, Leucine, Tyrosine, Phenylalanine, Cysteine, Macelignan, Citrus Unshiu Fruit Oil, Glutathione, Beta-Glucan, Lavandula Angustifolia (Lavender) Extract, Ocimum Basilicum (Basil) Extract, Althaea Officinalis Leaf/Root Extract, Houttuynia Cordata Extract, Anthemis Nobilis Flower Extract, Rosmarinus Officinalis (Rosemary) Leaf Extract, Foeniculum Vulgare (Fennel) Fruit Extract, Pyrus Malus (Apple) Fruit Water, Gleditschia Australis Thorn Extract, Angelica Dahurica Root Extract, Cimicifuga Racemosa Root Extract, Bletia Hyacinthina Bulb Extract, Oryza Sativa (Rice) Extract, Phaseolus Radiatus Seed Extract, Trichosanthes Kirilowii Root Extract, Amomum Xanthioides Seed Extract, Broussonetia Kazinoki Root Extract, Eugenia Caryophyllus (Clove) Flower Extract, Hydrolyzed Pea Protein, Lecithin, Olea Europaea (Olive) Fruit Oil, Squalane, Phytosterols, Butyrospermum Parkii (Shea) Butter, Punica Granatum Fruit Extract, Ficus Carica (Fig) Fruit Extract, Morus Alba Fruit Extract, Ginkgo Biloba Nut Extract, Lactobacillus/Soybean Ferment Extract, Salix Alba (Willow) Bark Extract, Cinnamomum Cassia Bark Extract, Origanum Vulgare Leaf Extract, Chamaecyparis Obtusa Leaf Extract, Scutellaria Baicalensis Root Extract, Stearic Acid, Sodium Acrylate/Sodium Acryloyldimethyl Taurate Copolymer, Arginine, PVM/MA Copolymer, Ammonium Acryloyldimethyltaurate/VP Copolymer, Isohexadecane, Polysorbate 80, Tocopheryl Acetate, Carbomer, Gardenia Florida Fruit Extract, Disodium EDTA